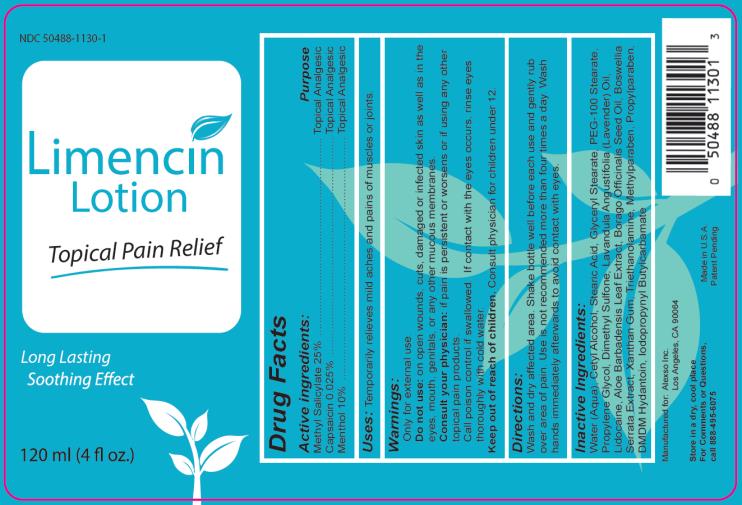 DRUG LABEL: Limencin
NDC: 50488-1130 | Form: LOTION
Manufacturer: Alexso, Inc.
Category: otc | Type: HUMAN OTC DRUG LABEL
Date: 20190212

ACTIVE INGREDIENTS: METHYL SALICYLATE 25 g/100 mL; CAPSAICIN 0.025 g/100 mL; MENTHOL 10 g/100 mL
INACTIVE INGREDIENTS: WATER; CETYL ALCOHOL; STEARIC ACID; GLYCERYL MONOSTEARATE; PEG-100 STEARATE; PROPYLENE GLYCOL; DIMETHYL SULFONE; LAVENDER OIL; LIDOCAINE; ALOE VERA LEAF; BORAGE SEED OIL; INDIAN FRANKINCENSE; XANTHAN GUM; TROLAMINE; METHYLPARABEN; PROPYLPARABEN; DMDM HYDANTOIN; IODOPROPYNYL BUTYLCARBAMATE

Limencin Lotion

Active ingredients:

Methyl Salicylate 25%
Capsaicin 0.025%
Menthol 10%

Purpose

Topical Analgesic

Uses:

Temporarily relieves mild aches and pains of muscles or joints.

Warnings:

Only for external use.

Do not use:

on open wounds, cuts, damaged or infected skin as well as in the eyes, mouth, genitals, or any other mucous membranes.

Consult your physician:

if pain is persistent or worsens or if using any other topical pain products.

Call poison control if swallowed. If contact with the eyes occurs, rinse eyes thoroughly with cold water.

Keep out of reach of children.

Consult physician for children under 12.

Directions

Wash and dry affected area. Shake bottle well before each use and gently rub over area of pain. Use is not recommended more than four times a day. Wash hands immediately afterwards to avoid contact with eyes.

Inactive ingredients

Water (Aqua), Cetyl Alcohol, Stearic Acid, Glyceryl Stearate, PEG-100 Stearate, Propylene Glycol, Dimethyl Sulfone, Lavandula Angustifolia (Lavendar) Oil, Lidocaine, Aloe Barbadensis Leaf Extract, Borago Officinalis Seed Oil, Boswellia Serrata Extract, Xanthan Gum, Triethanolamine, Methylparaben, Propylparaben, DMDM Hydantoin, Iodopropynyl Butylcarbamate

PRINCIPAL DISPLAY PANEL

NDC 50488-1130-1

Limencin Lotion
Topical Pain Relief
Long Lasting
Soothing Effect
120 ml (4 fl oz.)

Manufactured for: Alexso, Inc.

Los Angeles, CA 90064

Store in a dry, cool place
For Comments or Questions,
call 888.495.6078

Made in the U.S.A.
Patent Pending

Label